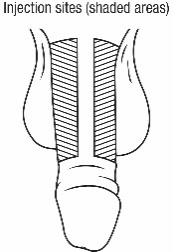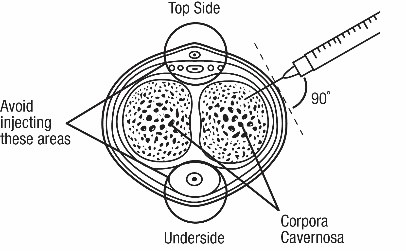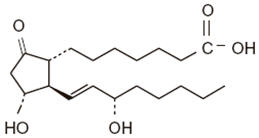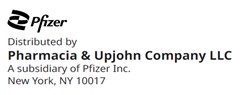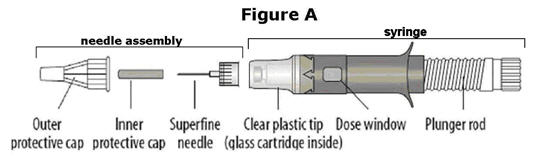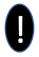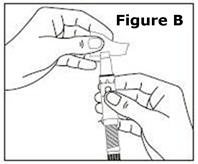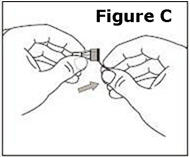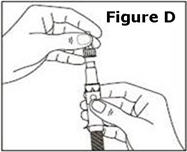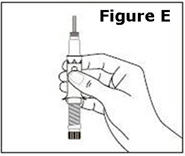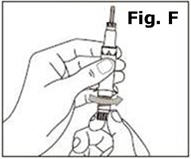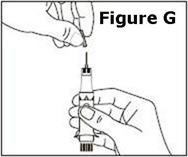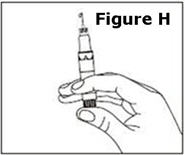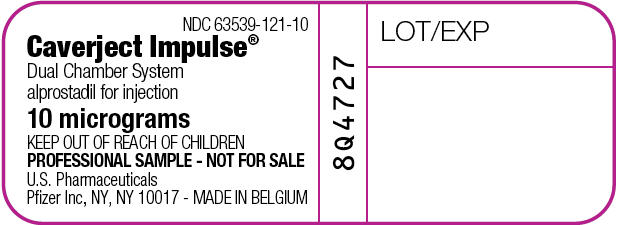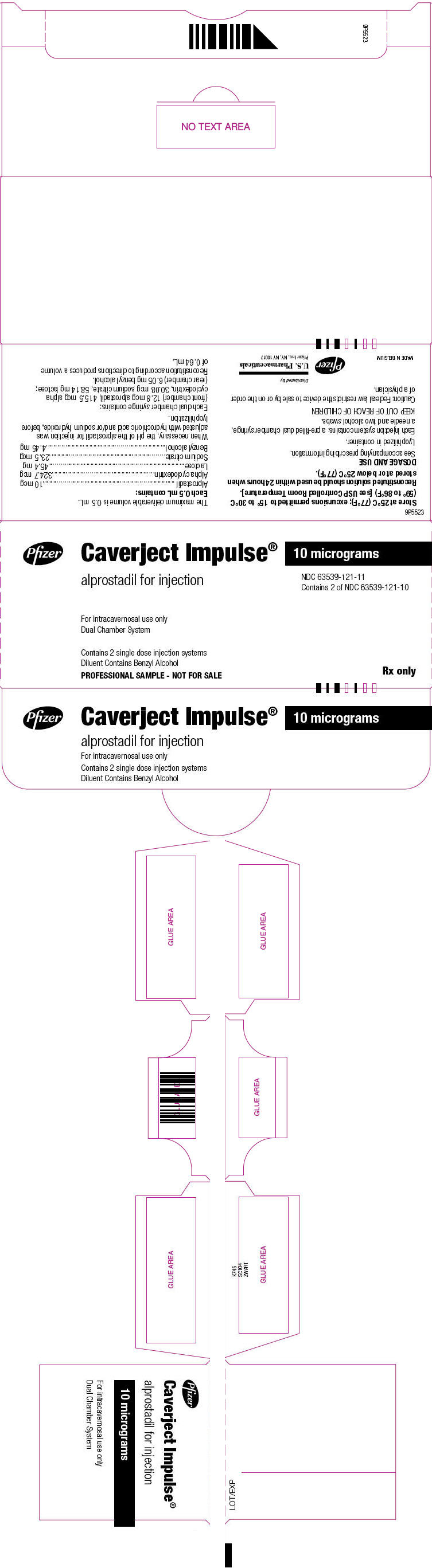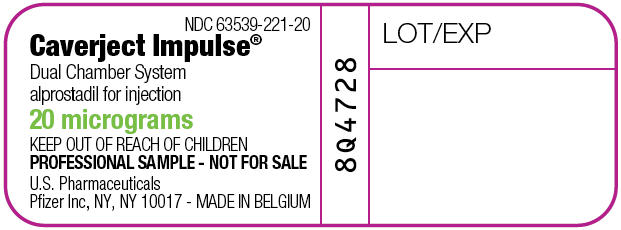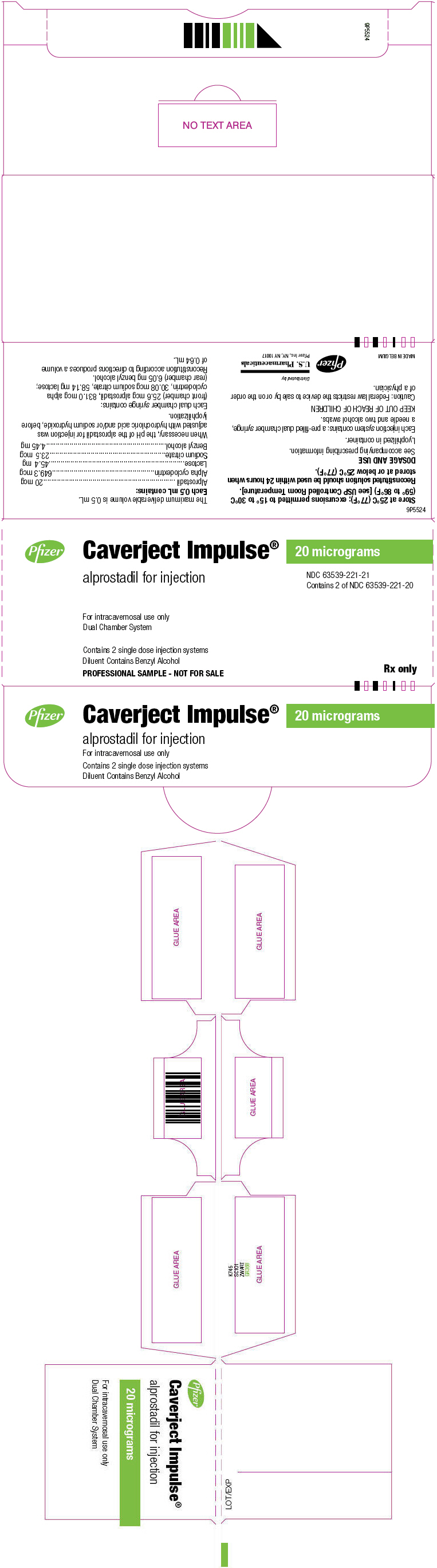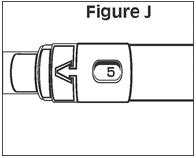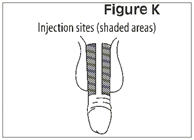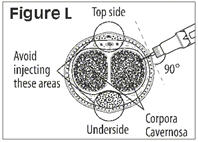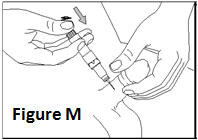 DRUG LABEL: Caverject Impulse
NDC: 63539-121 | Form: INJECTION, POWDER, LYOPHILIZED, FOR SOLUTION
Manufacturer: U.S. Pharmaceuticals
Category: prescription | Type: HUMAN PRESCRIPTION DRUG LABEL
Date: 20240723

ACTIVE INGREDIENTS: ALPROSTADIL 10 ug/0.5 mL
INACTIVE INGREDIENTS: ALFADEX 324.7 ug/0.5 mL; LACTOSE, UNSPECIFIED FORM 45.4 mg/0.5 mL; SODIUM CITRATE, UNSPECIFIED FORM 23.5 ug/0.5 mL; BENZYL ALCOHOL 4.45 mg/0.5 mL; HYDROCHLORIC ACID; SODIUM HYDROXIDE; WATER

HIGHLIGHTS OF PRESCRIBING INFORMATION

These highlights do not include all the information needed to use CAVERJECT IMPULSE safely and effectively. See full prescribing information for CAVERJECT IMPULSE.
CAVERJECT IMPULSE® (alprostadil) for injection, for intracavernosal use
Initial U.S. Approval: 1981

1 INDICATIONS AND USAGE

CAVERJECT IMPULSE is a prostaglandin E1 agonist indicated

- For the treatment of erectile dysfunction (1.1)
- As an adjunct to other diagnostic tests in the diagnosis of erectile dysfunction (1.2).

2 DOSAGE AND ADMINISTRATION

- Determine the most suitable dose and presentation of CAVERJECT to use. Use a new syringe for each dose of CAVERJECT (2.1).
- Administer first intracavernosal injections in the health care provider’s office and titrate the dose for each patient to the lowest effective dose (2.1).
- Instruct the patient on proper use and assess that they are well trained in the self-injection technique prior to initiation of at-home use (2.1).
- Recommended dosage for erectile dysfunction (2.2):
  - Erectile dysfunction of vasculogenic, psychogenic, or mixed etiology:
    Initiate dosing with 2.5 mcg
  - Erectile dysfunction of pure neurogenic etiology (spinal cord injury):
    Initiate dosing with 1.25 mcg
- Follow dose titration procedures for each type of erectile dysfunction and determine the maintenance dosage for patient home use in the health care provider’s office (2.2).
- The recommended frequency of injection is no more than 3 times weekly, with at least 24 hours between each dose (2.2).
- While on self-injection treatment, the patient should visit the prescribing health care provider’s office every 3 months to assess the efficacy and safety of the therapy (2.1).
- Follow procedure for CAVERJECT IMPULSE syringe preparation (2.3).
- Follow the procedure for CAVERJECT IMPULSE administration (2.4).
- To diagnose erectile dysfunction (pharmacologic testing), inject CAVERJECT IMPULSE intracavernosally and monitor patients for the occurrence of an erection (2.2).

3 DOSAGE FORMS AND STRENGTHS

For injection: 10 mcg or 20 mcg freeze-dried powder for reconstitution in a dual-chamber syringe (3).

4 CONTRAINDICATIONS

- Known hypersensitivity to the drug (4).
- Men who have conditions that predispose them to priapism, such as sickle cell anemia or sickle cell trait, multiple myeloma, or leukemia (4).
- Treatment of erectile dysfunction in men with fibrotic conditions of the penis, such as anatomical deformation, angulation, cavernosal fibrosis, or Peyronie's disease (4).
- Men with penile implants (4).

5 WARNINGS AND PRECAUTIONS

- Prolonged erection and priapism have occurred in patients receiving CAVERJECT. To minimize the chances of this occurring, titrate CAVERJECT IMPULSE slowly to the lowest effective dose (2.1). Advise patients to seek immediate medical assistance for an erection that persists longer than 4 hours (5.1).
- Penile fibrosis has occurred in patients receiving CAVERJECT. Follow patients regularly to detect signs of penile fibrosis. Discontinue in patients who develop penile angulation or cavernosal fibrosis (5.2).
- Hypotension - injections of CAVERJECT IMPULSE can lead to increased peripheral blood levels of alprostadil, especially in patients with significant corpora cavernosa venous leakage. Avoid use in patients with known cavernosal venous leakage (5.3).
- Injection site bleeding may occur in patients taking anticoagulants, such as warfarin or heparin. Compress the site of injection with an alcohol swab or sterile gauze for 5 minutes (5.4).
- Cardiovascular risk related to underlying medical conditions - Underlying treatable medical causes of erectile dysfunction should be diagnosed and treated prior to initiation of therapy (5.5).
- Risks of use in combination with other vasoactive medications injected intracavernosally - Safety and efficacy of combinations of CAVERJECT and other vasoactive agents have not been systematically studied. Use of such combinations is not recommended (5.6).
- Risk of needle breakage – A superfine needle is used for CAVERJECT IMPULSE and cases of needle breakage have been reported. Careful instruction in proper patient handling and injection techniques may minimize this risk (5.7).
- Benzyl alcohol – Serious and fatal adverse reactions can occur in neonates and low birth weight infants treated with benzyl alcohol-preserved formulations in infusion solutions, including CAVERJECT IMPULSE. CAVERJECT IMPULSE is not indicated in neonates and infants (5.8).
- Counsel patients about sexually transmitted diseases. Counsel patients about the protective measures necessary to guard against sexually transmitted disease including the Human Immunodeficiency Virus (HIV) (5.9).

6 ADVERSE REACTIONS

Most common (≥10%) adverse reactions: penile pain (6.1).

To report SUSPECTED ADVERSE REACTIONS, contact Pfizer at (1-800-438-1985 and www.pfizer.com) or FDA at 1-800-FDA-1088 or http://www.fda.gov/medwatch.

FULL PRESCRIBING INFORMATION

1 INDICATIONS AND USAGE

1.1 Erectile Dysfunction

CAVERJECT IMPULSE is indicated for the treatment of erectile dysfunction.

1.2 Diagnostic Test

CAVERJECT IMPULSE is indicated as an adjunct to other diagnostic tests in the diagnosis of erectile dysfunction.

2 DOSAGE AND ADMINISTRATION

2.1 Important Dosage and Administration Instructions

- Alprostadil is available in different strengths and presentations. Determine the most suitable dose and presentation for each patient. Use a new syringe for each dose of CAVERJECT.
- Titrate the dose of CAVERJECT IMPULSE for each patient to the lowest effective dose.
- CAVERJECT IMPULSE doses greater than 60 mcg are not recommended.
- Administer the first doses of CAVERJECT IMPULSE in the health care provider’s office by medically trained personnel.
- Instruct the patient on proper use and assess that they are well trained in the self-injection technique prior to initiation of home use. Refer to the Patient Information and Instructions for Use.
- Re-evaluate patients regularly (every 3 months or as clinically appropriate) and determine if dosage adjustments are needed.

2.2 Recommended Dosage for Erectile Dysfunction

Erectile Dysfunction of Vasculogenic, Psychogenic, or Mixed Etiology.

- Initiate dosing with 2.5 mcg of CAVERJECT IMPULSE intracavernousally as recommended [see Dosage and Administration 2.4].
- If there is a partial response at 2.5 mcg, administer another dose of 2.5 mcg within 1 hour.
- During titration, no more than 2 doses should be given within a 24-hour period.
- If additional titration is required, administer doses in increments of 5 to 10 mcg at least 24 hours apart.
- The optimal dose should produce an erection suitable for intercourse that does not exceed a duration of 1 hour.
- The patient must stay in the health care provider’s office until complete detumescence occurs.

Repeat the titration as necessary until the optimal dose is achieved. Doses greater than 60 mcg are not recommended.

Erectile Dysfunction of Pure Neurogenic Etiology (Spinal Cord Injury):

- Initiate dosing with 1.25 mcg of alprostadil using CAVERJECT.
- If there is a partial response, administer another dose of CAVERJECT of 1.25 mcg within 1 hour.
- No more than 2 doses during initial titration should be given within a 24-hour period.
- If additional titration is required, administer a dose of 5 mcg at least 24 hours later.
- The optimal dose should produce an erection suitable for intercourse that does not exceed a duration of 1 hour.
- The patient must stay in the health care provider’s office until complete detumescence occurs.

Repeat the titration as necessary until the optimal dose is achieved. Doses greater than 60 mcg are not recommended.

Maintenance Dosage for Patient Home Use:

- Once the dose of CAVERJECT IMPULSE has been determined in the health care provider’s office, additional dose adjustment may be required after consultation with the health care provider. Adjust the dose in accordance with the titration guidelines described above.
- The recommended frequency of injection is no more than 3 times weekly, with at least 24 hours between each dose.

Adjunct to the Diagnosis of Erectile Dysfunction

To diagnose erectile dysfunction (pharmacologic testing), inject CAVERJECT IMPULSE intracavernosally and monitor patients for the occurrence of an erection. Extensions of this testing are the use of CAVERJECT as an adjunct to laboratory investigations, such as duplex or Doppler imaging. For any of these tests, use a single dose of CAVERJECT IMPULSE that induces a rigid erection. Use the dose regimen for ‘Erectile Dysfunction of Vasculogenic, Psychogenic, or Mixed Etiology’ above.

2.3 Syringe Preparation Instructions

1. Select the CAVERJECT IMPULSE syringe based upon dose to be administered.

Syringe Strength | Reconstituted Concentration | Dosages Available for Delivery after Reconstitution
10 mcg | 10 mcg/0.5 mL | 2.5 mcg | 5 mcg | 7.5 mcg | 10 mcg
20 mcg | 20 mcg/0.5 mL | 5 mcg | 10 mcg | 15 mcg | 20 mcg

2. Open the sealed plastic tray. Remove the syringe, the needle assembly, and the alcohol swabs from the tray. The syringe has a dose window and a plunger. The needle assembly is a sealed unit that contains the outer protective cap, the inner protective cap, and the superfine needle.
3. Use the alcohol swab to wipe the rubber membrane at the tip of the syringe. Pick up the needle assembly, grasp the paper tab, and peel off the paper cover (the lid).
4. Hold the needle assembly by the cap and press the needle assembly onto the tip of the syringe. Turn it clockwise until the needle assembly is firmly locked into place.
5. Remove the outer protective cap from the needle by twisting it clockwise. Do not yet remove the inner protective cap, the thin plastic tube that directly covers the needle.
6. Hold the syringe system with the needle pointing upward. The plunger rod should still be in the fully extended position, with all of the threads visible. Slowly rotate the plunger rod clockwise until it goes all the way in and stops. Do not push on the plunger while trying to rotate it.
7. Turn the syringe upside down several times to make sure the solution is evenly mixed. The solution should be clear. Parenteral drug products should be inspected visually for particulate matter and discoloration prior to administration. The product should not be used if particulate matter or discoloration are present.
8. Hold the syringe with the needle upward and carefully remove the inner protective cap from the needle. Lightly tap the glass cartridge a few times with your finger until any large bubbles disappear up into the tip. With the syringe pointed upward, push in the plunger rod until it stops to push any air out.
9. To set the dose: locate the dose window on the syringe and then slowly turn the plunger rod clockwise until the correct dose number appears in the center of the window. The syringe is now ready for use. If you pass the correct number, keep turning the plunger in the same direction until the correct number comes around again – do not try to turn it backward.
10. After reconstitution, the syringe should be used within 24 hours when stored between 36 to 77°F (2°C to 25°C). Do not freeze. CAVERJECT IMPULSE is for single use only. Discard the injection delivery system and any remaining solution after use.

2.4 Administration Instructions

- Administer CAVERJECT IMPUSLE intracavernosally along the dorso-lateral aspect of the proximal third of the penis. See Figures A and B below.

Figure A

Figure B

- Wipe the intended injection site with an alcohol swab prior to injection.
- Avoid visible veins during injection.
- Alternate the side of the penis that is injected and the site of injection.
- Compress the site of injection with an alcohol swab or sterile gauze for 5 minutes.
- Each CAVERJECT IMPULSE syringe is intended for single use only (one dose only) and should be discarded after use.

3 DOSAGE FORMS AND STRENGTHS

Caverject Impulse (alprostadil) for injection contains sterile, freeze-dried alprostadil for reconstitution and sterile bacteriostatic water in a prefilled dual chamber glass cartridge. It is available in 10 mcg and 20 mcg strengths.

For injection: 10 mcg and 20 mcg of alprostadil freeze-dried powder for reconstitution in single-dose, pre‑filled, dual chambered glass cartridge syringe. The front chamber contains alprostadil and the rear chamber contains sterile bacteriostatic water. A 29 gauge needle system is also included.

The reconstituted solution is clear.

4 CONTRAINDICATIONS

CAVERJECT IMPULSE is contraindicated:

- in men who have a known hypersensitivity to the drug [see Adverse Reactions (6.1)]
- in men who have conditions that predispose them to priapism, such as sickle cell anemia or sickle cell trait, multiple myeloma, or leukemia [see Warnings and Precautions (5.1)]
- for the treatment of erectile dysfunction in men with fibrotic conditions of the penis, such as anatomical deformation, angulation, cavernosal fibrosis, or Peyronie's disease [see Warnings and Precautions (5.2)]
- in men with penile implants.

5 WARNINGS AND PRECAUTIONS

5.1 Prolonged Erection and Priapism

Prolonged erection, defined as erection lasting between 4 to 6 hours in duration, occurred in 4% of 1,861 patients treated up to 18 months in studies of CAVERJECT. The incidence of priapism (erections lasting more than 6 hours in duration) was 0.4%. In the event of an erection that persists longer than 4 hours, the patient should seek immediate medical assistance. If priapism is not treated immediately, penile tissue damage and permanent loss of potency may result.

To minimize the chances of prolonged erection or priapism, titrate CAVERJECT IMPULSE to the lowest effective dose [see Dosage and Administration (2.1]. In addition, do not use CAVERJECT IMPULSE in patients who have conditions that predispose them to priapism, such as sickle cell anemia or sickle cell trait, multiple myeloma, or leukemia [see Contraindications (4)].

5.2 Penile Fibrosis

The overall incidence of penile fibrosis reported in clinical studies with CAVERJECT was 3%. In one self-injection clinical study where duration of use was up to 18 months, the incidence of penile fibrosis was 7.8%.

Physical examination of the penis should be performed periodically to detect signs of penile fibrosis. Treatment with CAVERJECT IMPULSE should be discontinued in patients who develop penile angulation or cavernosal fibrosis.

5.3 Hypotension

Intracavernous injections of CAVERJECT IMPULSE can increase peripheral blood levels of alprostadil which can result in hypotension. Avoid use of CAVERJECT IMPULSE in patients with known cavernosal venous leakage.

5.4 Injection Site Bleeding When Used with Anticoagulants

Patients on anticoagulants, such as warfarin or heparin, may have increased propensity for injection site bleeding after intracavernosal injection with CAVERJECT IMPULSE. Compress the site of injection with an alcohol swab or sterile gauze for 5 minutes.

5.5 Cardiovascular Risk Related to Underlying Medical Conditions

There is a potential for cardiac risk of sexual activity in patients with preexisting cardiovascular disease. Therefore, treatments for erectile dysfunction, including CAVERJECT IMPULSE, generally should not be used in men for whom sexual activity is inadvisable because of their underlying cardiovascular status. In addition, the evaluation of erectile dysfunction should include a determination of potential underlying causes and the identification of appropriate treatment following a complete medical assessment.

5.6 Risks of Use in Combination with Other Vasoactive Medications Injected Intracavernosally

The safety and efficacy of combinations of CAVERJECT IMPULSE and other vasoactive agents injected intracavernosally have not been established in clinical studies. The risks of prolonged erection, priapism, and hypotension may be increased.

5.7 Needle Breakage

CAVERJECT IMPULSE uses a superfine (29 gauge) needle for administration. As with all superfine needles, the possibility of needle breakage exists. Needle breakage, with a portion of the needle remaining in the penis, has been reported and, in some cases, has required hospitalization and surgical removal. Careful instruction in proper patient handling and injection techniques may minimize the potential for needle breakage [see Dosage and Administration (2.3) and Adverse Reactions (6.2)].

5.8 Risk of Serious Adverse Reactions in Infants due to Benzyl Alcohol

The preservative benzyl alcohol contained in CAVERJECT IMPULSE has been associated with serious adverse events, including the "gasping syndrome", and death in pediatric patients. The minimum amount of benzyl alcohol at which toxicity may occur is not known. The risk of benzyl alcohol toxicity depends on the quantity administered and the liver and kidneys' capacity to detoxify the chemical. Premature and low-birth weight infants may be more likely to develop toxicity. CAVERJECT IMPULSE is not indicated for use in pediatric patients.

5.9 Counsel Patients About Sexually Transmitted Diseases

The use of CAVERJECT IMPULSE offers no protection against sexually transmitted diseases. Counsel patients about the protective measures necessary to guard against sexually transmitted diseases, including the Human Immunodeficiency Virus (HIV).

6 ADVERSE REACTIONS

The following are discussed in more detail in other sections of the labeling:

- Prolonged Erection and Priapism [see Warnings and Precautions (5.1)]
- Penile Fibrosis [see Warnings and Precautions (5.2)]

6.1 Clinical Trials Experience

Because clinical trials are conducted under widely varying conditions, adverse reaction rates observed in the clinical trials of a drug cannot be directly compared to rates in the clinical trials of another drug and may not reflect the rates observed in clinical practice.

CAVERJECT IMPULSE was evaluated in 87 patients in an open-label crossover study of 6 weeks treatment duration that compared the formulation of alprostadil for injection contained in CAVERJECT IMPULSE with the formulation contained in CAVERJECT. Doses used in this study ranged from 2.5 mcg to 20 mcg. Adverse reactions reported for the CAVERJECT IMPULSE formulation included: penis disorder (4.6%), prolonged erection (1.1%), injection site erythema (1.1%), rash (1.1%), dizziness (1.1%), and hematospermia (1.1%). Penis disorder included penile pain, post-injection pain, and pain with erection.

CAVERJECT IMPULSE was also evaluated in 63 patients in a single-dose, double-blind, crossover study that compared CAVERJECT IMPULSE with CAVERJECT. Doses used in this study ranged from 2.5 mcg to 20 mcg. Adverse reactions reported for the CAVERJECT IMPULSE formulation included: penile pain (1.6%) and pruritus (1.6%).

In addition to the adverse reactions observed for CAVERJECT IMPULSE in these two studies, the following adverse reactions have been reported in clinical studies of CAVERJECT:

Local Adverse Reactions: Local adverse reactions derived from 1861 patients in clinical studies of CAVERJECT, including an 18-month, open-label study, are shown in Table 1.

Table 1. Local Adverse Reactions Reported by ≥ 1% of Patients Treated with CAVERJECT for up to 18 Months
Penile pain | 37%
Prolonged erection | 4%
Penile fibrosis | 3%
Injection site hematoma | 3%
Penis disorder [Penis disorder includes: numbness, irritation, sensitivity, pruritus, erythema, skin tear, discoloration, itching.] | 3%
Injection site ecchymosis | 2%
Penile rash | 1%
Penile edema | 1%

The following local adverse reactions were reported in < 1% of patients: injection site hemorrhage, injection site inflammation, injection site itching, injection site swelling, injection site edema, urethral bleeding, penile warmth, numbness, irritation, sensitivity, pruritus, erythema, painful erection, and abnormal ejaculation.

In these studies, no local adverse reactions were reported in the 294 patients who received placebo, except for penile pain (2%).

Penile Pain: In the majority of the cases, penile pain was rated mild or moderate in intensity. Three percent of patients discontinued treatment because of penile pain

Prolonged Erection/Priapism: Prolonged erection was defined as an erection that lasted for 4 to 6 hours; priapism was defined as an erection that lasted 6 hours or longer. In clinical studies, the frequency of prolonged erection after CAVERJECT was 4%, while the frequency of priapism was 0.4% [see Warnings and Precautions (5.1)].

Penile Hematoma/Ecchymosis: In clinical studies, the frequency of penile hematoma and ecchymosis was 3% and 2%, respectively.

Systemic Adverse Reactions: Systemic adverse reactions reported by ≥ 1% of subjects in clinical studies of CAVERJECT included: dizziness (1%).

The following systemic adverse reactions were reported in < 1% of patients: testicular pain, scrotal edema, hematuria, pelvic pain, hypotension, vasodilation, vasovagal reaction, diaphoresis, rash, and non-application site pruritus. Three patients (0.2%) discontinued due to symptomatic hypotension.

No systemic adverse reactions were reported in the 294 patients who received placebo.

6.2 Post-marketing Experience

The following additional adverse reactions have been reported during post approval use of CAVERJECT IMPULSE. Because these reactions are reported voluntarily from a population of uncertain size, it is not always possible to reliably estimate their frequency or establish a causal relationship to drug exposure.

Injury and procedural complication: device malfunction/failure, needle breakage, drug ineffective and drug effect decreased.

7 DRUG INTERACTIONS

The potential for pharmacokinetic drug-drug interactions between alprostadil and other agents administered orally or intracavernosally has not been formally studied [see Warnings and Precautions (5.6)].

8 USE IN SPECIFIC POPULATIONS

8.1 Pregnancy

CAVERJECT IMPULSE is not indicated for use in females.

8.2 Lactation

CAVERJECT IMPULSE is not indicated for use in females.

8.4 Pediatric Use

CAVERJECT IMPULSE is not indicated for use in pediatric patients [see Warnings and Precautions (5.8)].

8.5 Geriatric Use

A total of 341 subjects included in clinical studies were 65 and older. No overall differences in safety and effectiveness were observed between these subjects and younger subjects, and the other reported clinical experience has not identified differences in responses between elderly and younger patients.

10 OVERDOSAGE

Overdosage was not observed in clinical trials with CAVERJECT IMPULSE. If intracavernous overdose of CAVERJECT IMPULSE occurs, the patient should be under medical supervision until any systemic effects have resolved and/or until penile detumescence has occurred. Treatment of any systemic symptoms (e.g., hypotension) would be appropriate.

11 DESCRIPTION

CAVERJECT IMPULSE contains alprostadil a synthetic form of prostaglandin E1 (PGE1) and is designated chemically as (11α,13E,15S)-11,15-dihydroxy-9-oxoprost-13-en-1-oic acid. The molecular weight is 354.49.

Alprostadil is a white to off-white crystalline powder with a melting point between 115° and 116°C. Its solubility at 35°C is 8000 micrograms (mcg) per 100 milliliter double distilled water.

The structural formula of alprostadil is represented below:

CAVERJECT IMPULSE is available as a disposable, single-dose, dual chamber syringe system. The system includes a glass cartridge which contains sterile, freeze-dried alprostadil in the front chamber and sterile bacteriostatic water for injection in the rear chamber. The alprostadil is reconstituted with the sterile bacteriostatic water just before injection. CAVERJECT IMPULSE is available in two strengths for intracavernosal administration:

10 microgram – The reconstituted solution has a volume of 0.64 mL. The delivered volume, 0.5 mL, contains 10 micrograms (mcg) of alprostadil, 324.7 mcg of alpha cyclodextrin, 45.4 mg of lactose, 23.5 mcg of sodium citrate, and 4.45 mg of benzyl alcohol.

20 microgram – The reconstituted solution has a volume of 0.64 mL. The delivered volume, 0.5 mL, contains 20 micrograms (mcg) of alprostadil, 649.3 mcg of alpha cyclodextrin, 45.4 mg of lactose, 23.5 mcg of sodium citrate, and 4.45 mg of benzyl alcohol.

During manufacture, the pH of the alprostadil for injection was adjusted with hydrochloric acid and/or sodium hydroxide before lyophilization.

12 CLINICAL PHARMACOLOGY

12.1 Mechanism of Action

Alprostadil induces erection by relaxation of trabecular smooth muscle and by dilation of cavernosal arteries. This leads to expansion of lacunar spaces and entrapment of blood by compressing the venules against the tunica albuginea, a process referred to as the corporal veno-occlusive mechanism.

12.2 Pharmacodynamics

There are no results from pharmacodynamic studies in humans.

12.3 Pharmacokinetics

Absorption: For the treatment of erectile dysfunction, alprostadil is administered by injection into the corpora cavernosa. The absolute bioavailability of alprostadil has not been determined.

Distribution: Following intracavernosal injection of 20 mcg alprostadil, mean peripheral plasma concentrations of alprostadil at 30 and 60 minutes after injection (89 and 102 picograms/mL, respectively) were not significantly greater than baseline levels of endogenous alprostadil (96 picograms/mL). Plasma levels of alprostadil were measured using a radioimmunoassay method. Alprostadil is bound in plasma primarily to albumin (81% bound) and to a lesser extent α-globulin IV-4 fraction (55% bound). No significant binding to erythrocytes or white blood cells was observed.

Metabolism: Alprostadil is converted to compounds, which are further metabolized prior to excretion. Following intravenous administration, approximately 80% of circulating alprostadil is metabolized in one pass through the lungs, primarily by beta- and omega-oxidation. Following intracavernosal injection of 20 mcg alprostadil, peripheral levels of the major circulating metabolite, 13, 14-dihydro-15-oxo-PGE1, increased to reach a peak 30 minutes after injection and returned to pre-dose levels by 60 minutes after injection.

Excretion: The metabolites of alprostadil are excreted primarily by the kidney, with almost 90% of an administered intravenous dose excreted in urine within 24 hours post-dose. The remainder of the dose is excreted in the feces. There is no evidence of tissue retention of alprostadil or its metabolites following intravenous administration.

Pharmacokinetics in Specific Populations

Geriatric: The potential effect of age on the pharmacokinetics of alprostadil has not been formally evaluated.

Race: The potential effect of race on the pharmacokinetics of alprostadil has not been formally evaluated.

Renal and Hepatic Insufficiency: The pharmacokinetics of alprostadil have not been formally studied in patients with renal or hepatic insufficiency.

13 NONCLINICAL TOXICOLOGY

13.1 Carcinogenesis, Mutagenesis, Impairment of Fertility

Carcinogenesis

Long-term carcinogenicity studies have not been conducted.

Mutagenesis

The following battery of mutagenicity assays revealed no potential for mutagenesis: bacterial mutation (Ames), alkaline elution, rat micronucleus, sister chromatid exchange, CHO/HGPRT mammalian cell forward gene mutation, and unscheduled DNA synthesis (UDS).

Impairment of Fertility

Rat reproductive studies indicate that alprostadil at doses of up to 0.2 mg/kg/day does not adversely affect or alter male rat fertility. These doses are approximately 32-fold higher than the maximum recommended human dose of 60 mcg based on body surface area.

14 CLINICAL STUDIES

The efficacy of CAVERJECT IMPULSE was based upon clinical studies of CAVERJECT.

The efficacy of CAVERJECT was investigated in men with a diagnosis of erectile dysfunction due to psychogenic, vasculogenic, neurogenic, and/or mixed etiology in two double-blind placebo-controlled studies (Study 1 and Study 2) and in one 6-month open-label study (Study 3). In clinical studies (Study 1 and Study 3), over 80% of patients experienced an erection sufficient for sexual intercourse after intracavernosal injection of CAVERJECT.

Study 1: A total of 153 men with ED with a mean age of 53 years (range 23–69 years) were enrolled. The study had three phases: a 2.5 week, randomized, double-blind, placebo-controlled crossover phase in which each man received in-office injections of placebo or 2.5 mcg, 5 mcg, 7.5 mcg, or 10 mcg of CAVERJECT; a 2 week, open-label, in-office dose-titration phase to identify the optimum home-use dose (the latter dose was defined as a dose inducing an erection sufficient for intercourse and lasting ≤ 60 minutes); and a 4-week open-label, at-home phase. In the double-blind placebo-controlled, crossover phase, each dose of CAVERJECT was significantly more effective than placebo by clinical evaluation ("full penile rigidity") and by RigiScan criteria (≥ 70% rigidity for at least 10 minutes); there was no response to placebo. The percentage of responders increased with increasing doses of CAVERJECT. The overall response rates in the crossover and dose-titration phases were 76% (117/153) by clinical evaluation and 51% (78/152) by RigiScan criteria. Seventy-three percent of the injections in 102 men who used CAVERJECT in the at-home phase resulted in satisfactory intercourse. Seventy-five percent of the men who used CAVERJECT in the at-home phase remained on the dose identified as optimum for them during the dose-titration phase; 17% and 8% of the men decreased or increased their dose, respectively. The mean duration of erection per injection was 70.8 minutes.

Study 2: A total of 296 men with ED with a mean age of 54 years (range 21–74 years) were enrolled in this double-blind, placebo controlled, parallel-arm design study. The men were randomly assigned to one of five groups and received either a single dose of placebo, 2.5 mcg, 5 mcg, 10 mcg, or 20 mcg of CAVERJECT. No patient responded to placebo. The differences in the response rates in both the clinical and the RigiScan evaluations between each of the doses of CAVERJECT and placebo were statistically significant. There was also a statistically significant dose-response relationship with higher clinical response rates and higher RigiScan response rates with increasing doses of CAVERJECT (with exception of the 10-mcg dose). The mean duration of erection after injection ranged from 12 minutes after the 2.5-mcg dose to 44 minutes after the 20-mcg dose and the relationship was linear (p = .025, linear regression analysis).

Study 3: The efficacy of CAVERJECT was further evaluated in a 6-month, open-label, at-home study in 683 men with ED with a mean age of 58 years (range 20–79 years). The optimum dose of CAVERJECT was established by titration in 89% of men (606/683). A total of 471/683 men (69%) completed the 6-month study. Eighty-seven percent of the 13,762 injections of CAVERJECT administered resulted in satisfactory sexual activity. The mean duration of erection was 67.5 minutes.

The formulation of alprostadil contained in CAVERJECT IMPULSE was compared to CAVERJECT in 87 men with ED in a single-blind, crossover study. The doses used by the patients in the study ranged from 2.5 mcg to 20 mcg and were the same for both formulations. The efficacy of the two formulations was shown to be comparable, as assessed by the 30-point erectile function (EF) domain score from the International Index of Erectile Function (IIEF) and by a physician-assessment score for erectile response. The mean EF domain scores for CAVERJECT and CAVERJECT IMPULSE were 26.6 (SD=5.3) and 27.6 (SD=3.8), respectively. The mean physician's assessment scores for CAVERJECT and CAVERJECT IMPULSE were 2.6 (SD=0.6) and 2.7 (SD=0.5), respectively, based on a scale of 0 (no tumescence) to 3 (full rigidity).

16 HOW SUPPLIED/STORAGE AND HANDLING

CAVERJECT IMPULSE is supplied as a disposable, single-dose, dual chamber syringe system. The system includes a glass cartridge, which contains sterile, freeze-dried alprostadil in the front chamber and sterile bacteriostatic water for reconstitution in the rear chamber. The syringes contain either 12.8 or 25.6 mcg of alprostadil to allow delivery of a maximum of 10 or 20 mcg/0.5mL. Store the unreconstituted product at 68°F to 77°F (20°C to 25°C); excursions permitted to 59°F to 86°F (15°C to 30°C) [see USP Controlled Room Temperature].

When reconstituted and used as directed, the deliverable amount for the 10 mcg strength is 10 mcg/0.5 mL or an increment of 10 mcg/0.5 mL: 2.5 mcg/0.125 mL, 5 mcg/0.25 mL, or 7.5 mcg/0.375 mL of alprostadil. The deliverable amount for the 20 microgram strength is 20 mcg/0.5 mL or an increment of 20 mcg/0.5 mL: 5 mcg/ 0.125 mL, 10 mcg/0.250 mL, or 15 mcg/0.375 mL of alprostadil. The reconstituted solution should be used within 24 hours when stored between 36–77°F (2°C to 25°C). Do not freeze.

CAVERJECT IMPULSE is supplied in a carton containing 2 blister trays. Each blister tray contains one dual chamber syringe system, one needle and 2 alcohol swabs. It is available in the following strengths:

10 mcg | NDC 0009-5181-01
20 mcg | NDC 0009-5182-01

17 PATIENT COUNSELING INFORMATION

Advise the patient to read the FDA-approved patient labeling (Patient Information and Instructions for Use)

Dosing and Self-Administration

To ensure safe and effective use of CAVERJECT IMPULSE, instruct and train the patient in the self-injection technique before he begins treatment with CAVERJECT IMPULSE, at home. Inform the patient the initial dose administration and dose titration will take place in the health care provider’s office [see Dosage and Administration (2.1)].

Once the home dose of CAVERJECT IMPULSE has been established instruct the patient not to change the dose without consulting their health care provider.

The patient may expect an erection to occur within 5 to 20 minutes and it should last no longer than 1 hour. CAVERJECT IMPULSE should be used no more than 3 times per week, with at least 24 hours between each use.

Inform the patient that they must visit the health care provider’s office for regular check-ups for assessment of the therapeutic benefit and safety of treatment with CAVERJECT IMPULSE.

When self-administering the patient should be instructed to [see Dosage and Administration (2.3, 2.4)]:

- Discard any reconstituted solution with precipitates or discoloration
- Administer the injection along the dorso-lateral aspect of the proximal third of the penis
- Wipe the intended injection site with an alcohol swab prior to injection
- Avoid visible veins during injection
- Alternate the side of the penis that is injected and the site of injection
- Compress the site of injection with an alcohol swab or sterile gauze for 5 minutes
- Use each CAVERJECT IMPULSE system only once and discard after use
- Not use a bent needle. Do not attempt to straighten a bent needle. Remove the needle from the syringe, discard it, and attach a new, unused sterile needle to the syringe
- Not re-use or share needles and to properly discard after use.

Needle Breakage

Advise patients that needle breakage has occurred during self-injection of CAVERJECT. Advise patients to insert the needle perpendicular to the long axis of the penis to avoid bending or breakage of the needle [see Warnings and Precautions (5.7) and Adverse Reactions (6.2)].

Penile Pain

Advise patients that the most frequently occurring side-effect is penile pain after injection and is usually mild to moderate in severity [see Adverse Reactions (6.1)].

Priapism

A potentially serious adverse reaction with CAVERJECT IMPULSE is priapism. Instruct the patient to seek immediate medical assistance if an erection persists for longer than 4 hours [see Warnings and Precautions (5.1)].

Penile Fibrosis

Penile fibrosis has been reported in clinical studies with CAVERJECT. Advise the patient to report any penile pain that was not present before or that increased in intensity, as well as the occurrence of nodules or hard tissue in the penis or curvature of the erect penis to his physician as soon as possible. [see Warnings and Precautions (5.2)].

Injection Site Reactions

Inform the patient that injection of CAVERJECT IMPULSE can induce a small amount of bleeding at the site of injection and that hematoma and ecchymosis may occur. Advise the patient to report any persistent redness, tenderness or swelling [see Warnings and Precautions (5.4)].

Sexually Transmitted Disease

Use of CAVERJECT IMPULSE offers no protection from the transmission of sexually transmitted diseases. Advise the patient about the protective measures that are necessary to guard against the spread of sexually transmitted diseases, including the human immunodeficiency virus (HIV) [see Warnings and Precautions (5.9)].

This product's label may have been updated. For current full prescribing information, please visit www.pfizer.com

LAB-0007-10.0

Patient Information

CAVERJECT IMPULSE® [KAV-er-jeckt]

(alprostadil)
for injection, for intracavernosal use

Read this Patient Information before you start using CAVERJECT IMPULSE and each time you get a refill. There may be new information. This information does not take the place of talking to your healthcare provider about your medical condition or your treatment.

What is CAVERJECT IMPULSE?

CAVERJECT IMPULSE is a prescription medicine used:

- to treat erectile dysfunction (ED).
- with other medical tests to diagnose ED.

CAVERJECT IMPULSE is not meant for use in women or children under 18 years of age.

Do not use CAVERJECT IMPULSE if you:

- are allergic to alprostadil or any of the ingredients in CAVERJECT. See the end of this leaflet for a complete list of ingredients in CAVERJECT.
- have certain medical problems that might cause you to have an erection that lasts for more than 4 hours, such as sickle cell anemia, sickle cell trait, multiple myeloma, leukemia.
- have a deformed penis shape
- have a penile implant

Before you use CAVERJECT IMPULSE, tell your healthcare provider if you:

- have had an erection that lasted more than 4 hours
- have sickle cell trait or sickle cell anemia
- have or have had a blood cell cancer called multiple myeloma or leukemia
- have a deformed penis shape
- have a penile implant
- have low blood pressure (hypotension)
- have bleeding problems
- have or have had heart problems such as a heart attack, irregular heartbeat, angina, chest pain, narrowing of the aortic valve or heart failure
- have any other medical conditions

Tell your healthcare provider about all the medicines you take, including prescription and over-the-counter medicines, vitamins, and herbal supplements.

CAVERJECT IMPULSE may affect the way other medicines work, and other medicines may affect the way CAVERJECT IMPULSE works causing side effects.

Especially tell your healthcare provider if you take any other medicines that are injected into your penis (intracavernosally) or certain medicines called anticoagulant medicines (such as heparin or warfarin).

Ask your healthcare provider or pharmacist for a list of these medicines, if you are not sure.

Know the medicines you take. Keep a list of them to show to your healthcare provider and pharmacist when you get a new medicine.

How should I use CAVERJECT IMPULSE?

- See the detailed Instructions for Use that comes with your CAVERJECT IMPULSE for information about how to prepare and inject CAVERJECT IMPULSE the right way.
- Use CAVERJECT IMPULSE exactly as your healthcare provider tells you to.
- Your healthcare provider will tell you how much CAVERJECT IMPULSE to use and when to use it.
- Your healthcare provider may change your dose if needed. Do not change your dose of CAVERJECT IMPULSE without first talking to your healthcare provider.
- Your healthcare provider should show you how to prepare and inject CAVERJECT IMPULSE the right way before you inject it for the first time.
- CAVERJECT IMPULSE should not be used more than 3 times per week.
- CAVERJECT IMPULSE should not be used more than 1 time every 24 hours.
- Change the exact place and side of the penis that you inject Caverject Impulse each time you use it.
- CAVERJECT IMPULSE is for one use only and should be thrown away properly after a single use.

You should see your healthcare provider every 3 months for check-ups to be sure that CAVERJECT IMPULSE is working the right way and to change your CAVERJECT IMPULSE dose if needed.

What are the possible side effects of CAVERJECT IMPULSE?

CAVERJECT IMPULSE may cause serious side effects, including:

- an erection that will not go away. If you have an erection that lasts more than 4 hours, get medical help right away. If it is not treated right away, this condition can permanently damage your penis.
- deformed penis shape (penile fibrosis). Your healthcare provider should check your penis regularly for signs of penile fibrosis. You should not continue to use CAVERJECT IMPULSE if you get penile fibrosis.
- low blood pressure (hypotension)
- injection site bleeding. People who take certain medicines called anticoagulants (such as heparin or warfarin) may have a risk for increased bleeding at the injection site.
- increased risk of heart problems. Sexual activity can put an extra strain on your heart, especially if your heart is weak from a heart attack or heart disease. Ask your healthcare provider if your heart is healthy enough to handle the extra strain of having sex. Stop sexual activity and get medical help right away if you get symptoms of a heart problem such as chest pain, dizziness or nausea.
- needle breakage. There is a possibility of needle breakage with use of CAVERJECT IMPULSE. To best avoid breaking the needle, you should pay careful attention to your healthcare provider's instructions and handle the syringe and needle properly. If the needle is bent at any time, do not attempt to straighten it and do not use it. A bent and re-straightened needle is more likely to break. Remove the needle from the syringe, discard, and attach a new, unused sterile needle to the syringe. If the needle breaks during injection and you are able to see and grasp the broken end, you should remove it and contact your healthcare provider. If you cannot see or cannot grasp the broken end, you should promptly contact your healthcare provider.
- benzyl alcohol toxicity. Benzyl alcohol is a preservative in CAVERJECT IMPULSE. Benzyl alcohol has caused serious side effects, including death, in children, especially premature and low-birth weight infants, who have received the preservative benzyl alcohol. CAVERJECT IMPULSE is not meant for use in children.

CAVERJECT IMPULSE does not protect you or your partner from getting sexually transmitted infections, including HIV-the virus that causes AIDS.

The most common side effects of CAVERJECT IMPULSE include:

- penile pain

These are not all the possible side effects of CAVERJECT IMPULSE.

Call your doctor for medical advice about side effects. You may report side effects to FDA at 1-800-FDA-1088.

General information about the safe and effective use of CAVERJECT IMPULSE

Medicines are sometimes prescribed for purposes other than those listed in a Patient Information Leaflet. Do not use CAVERJECT IMPULSE for a condition for which it was not prescribed. Do not give CAVERJECT IMPULSE to other people even if they have the same symptoms that you have. It may harm them.

You can ask your pharmacist or healthcare provider for information about CAVERJECT IMPULSE that is written for health professionals.

What are the Ingredients in CAVERJECT IMPULSE?

Active ingredient: alprostadil

Inactive ingredients: alpha cyclodextrin, lactose, sodium citrate, benzyl alcohol and hydrochloric and/or sodium hydroxide for pH adjustment.

This product’s label may have been updated. For current full prescribing information, please visit www.pfizer.com

LAB-0641-8.0

Revised January 2023

INSTRUCTIONS FOR USE CAVERJECT [KAV-er-jeckt]® (alprostadil) for injection, for intracavernosal use

Before you use CAVERJECT, your doctor must train you in how to prepare and give the injection properly.

Before using CAVERJECT, talk to your doctor about what to expect when using it, possible side effects, and what to do if side effects occur. Your dose has been selected for your individual needs. Do not change your dose without consulting your doctor. If you are not sure of the volume or dose to be used, talk to your doctor or pharmacist.

Follow these instructions exactly to properly prepare the syringe for use, and to correctly inject a sterile (germ-free) dose of CAVERJECT.

Supplies Needed

The CAVERJECT IMPULSE carton contains two (2) sealed plastic trays, with one dose of Caverject in each tray.

Each tray contains: (a) a syringe, (b) a separate needle assembly and (c) two alcohol swabs. The syringe and the needle assembly are shown in Figure A (below). Please note that the needle assembly is packaged as a single piece and is sealed with a paper cover on the bottom.

DO NOT try to assemble the syringe until you have read ALL of the instructions.

First-read through ALL of the instructions (Step 1 through Step 12) before trying to assemble the syringe. Then go back to Step 1 and begin to prepare the syringe for use.

CAVERJECT IMPULSE is available in two versions: the 10 mcg strength (white plunger) and the 20 mcg strength (blue plunger). Each syringe is designed to be used only one time, but you can select the dose that will be delivered:

- The 10 mcg strength syringe (white plunger) can deliver 10 mcg (the full dose), or one of three partial doses: 7.5 mcg, or 5 mcg, or 2.5 mcg.
- The 20 mcg strength syringe (blue plunger) can deliver 20 mcg (the full dose), or one of three partial doses: 15 mcg, or 10 mcg, or 5 mcg.

If you deliver a partial dose there will be left-over solution in the syringe – this is normal.

MAKE SURE YOU HAVE THE CORRECT STRENGTH OF CAVERJECT IMPULSE to deliver your assigned dose

INSTRUCTIONS for PREPARING the SYRINGE (Step 1 through Step 12)

Wash your hands thoroughly and dry them with a clean towel.

STEP 1.

Open the sealed plastic tray. Remove the syringe, the needle assembly, and the alcohol swabs from the tray. All items should be present.

Look at the needle assembly. The needle assembly is a sealed unit that contains the outer protective cap, the inner protective cap, and the superfine needle, as shown in Figure A. It is sealed with a small round paper cover (not shown in Figure A).

Do not open the needle assembly at this point – leave it sealed inside the outer protective cap.

Next, examine the syringe. Find the location of the dose window. Right now you will not see anything in this window, but at a later Step, a number will appear in this window (the dose to be delivered).

Finally, look at the Plunger, but do not move it at this time. During the assembly process, some Steps may ask you to ROTATE the plunger and other steps may ask you to PUSH the plunger.

It is important to only rotate the plunger – or only push – as directed in each Step, but DO NOT do both at the same time.

Never PUSH on the plunger – even slightly – while trying to rotate it. This can cause the plastic threads on the plunger rod to stick.

 | STEP 2. | Open the packet containing the alcohol swab, and then pick up the syringe. Use the alcohol swab to wipe the rubber membrane at the tip of the syringe (Figure B). Discard the alcohol swab.
 | STEP 3. | Pick up the Needle Assembly. Grab the paper tab and peel off the paper cover (lid) from the bottom of the needle assembly (Figure C).
 | STEP 4. | Hold the needle assembly by the cap. Pick up the syringe with your other hand. Press the needle assembly onto the tip of the syringe and turn it clockwise (like tightening a screw) until the needle assembly is firmly locked into place. Remove (twist off - clockwise) the outer protective cap from the needle (Figure D), but DO NOT REMOVE the inner protective cap at this time. The inner protective cap is the thin plastic tube that directly covers the needle. It will be removed later. If you are not sure which piece is the inner protective cap, see Figure A (Step 1) to identify the inner protective cap.
 | STEP 5. | The next few steps will mix the powder and the fluid to make the Caverject Impulse solution. Hold the syringe system with the needle pointing upward. The plunger rod should still be in the fully extended position, with all of the threads visible, as shown in Figure E.
 | STEP 6. | Slowly ROTATE the plunger rod clockwise (like tightening a screw,) until it goes all the way in and stops (Figure F). This automatically combines the drug powder and the fluid.
 |  |  | DO NOT turn the plunger rod counter-clockwise (do not try to "unscrew" the plunger rod).
 |  |  | DO NOT PUSH on the plunger while trying to rotate it. This can cause the plastic threads on the plunger rod to stick.
 | STEP 7. | Turn the syringe upside down several times to make sure the solution is evenly mixed. The solution should be clear. Do not use it if it is cloudy or contains particles.
 | STEP 8. STEP 9. | Hold the syringe with the needle upward and carefully remove the inner protective cap from the needle (Figure G). Do not touch the exposed needle because it is sterile. Next, you need to remove any large bubbles from the solution. Lightly tap the glass cartridge a few times with your finger until any large bubbles disappear up into the tip. Very small bubbles may remain.
 | STEP 10. | With the syringe pointed upward (Figure H), use your thumb to push in the plunger rod until it stops. This will push the air out. Some liquid will appear at the needle point. After pressing the plunger you may still see some small bubbles on the wall of the glass cartridge. This is normal.
 |  |  | If you can't press the plunger rod in, check that the plunger rod is rotated all the way: turn it clockwise until it stops, and then repeat Step 10.
 |  |  | After the plunger is pushed in – Do Not rotate the plunger. That will be done in the next step.
 | STEP 11. | PLEASE READ the following before going on. In Step 11, you will need to set the dose by ROTATING the plunger until the correct dose appears in the small oval Dose Window on the syringe. The plunger must be rotated "clock-wise" – like tightening a screw.
 |  |  | DO NOT PUSH on the plunger while trying to rotate it. This can cause the plastic threads on the plunger rod to stick. If the plunger does stick, you can try to free it by gently turning it backward ("unscrewing it") and trying again.
 |  | TO SET THE DOSE: Locate the Dose Window on the syringe. This small oval window (above the left thumb in Figure I) is where the dose number will appear when the plunger is rotated. Then – holding the syringe as shown in Figure I, slowly turn the plunger rod clockwise (like tightening a screw – see arrow in Figure I) until the correct dose number appears in the center of the window (Figure J). If you pass the correct number, keep turning the plunger in the same direction until the correct number comes around again – do not try to turn it backward

STEP 12. | The syringe is now ready for use. Set the syringe down on a flat level surface. The needle is sterile. Make sure the needle does not touch the surface or anything else.

How to give the injection

- Make yourself comfortable. Take some time to relax yourself and your partner. If your doctor has recommended you use an alcohol cleansing swab, open one now.
- Make sure that the needle is not bent. If it is, do not use it. Do not attempt to straighten the needle out. Properly discard it.

1. The injection will go into the part of the penis shown as the shaded area in Figure K. Do not inject into the white areas because there may be blood vessels in the white areas. Also see Figure L.

2. The correct injection angle is shown in Figure L.
3. If your doctor has recommended that you use an alcohol swab, wipe over the area for injection and let it dry. Reconfirm that the correct dose is visible in the dose window. If the correct dose is not in the dose window, repeat Step 11.

4. Take hold of the penis from the front, with the first two fingers underneath close to the testicles and the thumb on top (Figure M).
5. Gently squeeze the penis between your thumb and finger so that the injection site bulges out. If there is a foreskin on the penis, make sure it is stretched.
6. Keeping a firm grip on the penis and taking the syringe in your free hand, push the needle straight through the skin all the way into the bulgy part (corpora cavernosa). Avoid veins or other obvious blood vessels (Figures K and L).
7. Push the plunger firmly and steadily until it no longer moves. Plunger movement may be very small or undetectable if administering a partial dose.
8. If the plunger does not move easily adjust the needle depth slightly and try again. Do not force the solution from the syringe.
9. After completing the injection, carefully pull the needle out. A drop of liquid may remain on the tip of the needle. Press gently on the injection site with the alcohol swab. Massage the penis to help the Caverject Impulse solution spread through it.

Some liquid will remain in the syringe if you delivered a PARTIAL dose. This is expected. Do not try to inject left-over liquid from a partial dose. Syringes used to inject a partial dose must be discarded since each syringe can only be used one time. Discard syringes with left-over liquid.

  - A partial dose is 5 mcg, 10 mcg or 15 mcg for the BLUE plunger syringe.
  - A partial dose is 2.5 mcg, 5 mcg, or 7.5 mcg for the WHITE plunger syringe.

Do not keep any solution in the cartridge to use for a second injection. When you have finished with the syringe, discard it carefully as recommended by your doctor, so no one will use it or stick themselves with it.

After your injection:

Dispose of your used CAVERJECT IMPULSE syringes and needle.

- Put your used CAVERJECT IMPULSE syringe and needle in a FDA-cleared sharps disposal container right away after use. Do not throw away (dispose of) loose needles and syringes in your household trash.
- If you do not have a FDA-cleared sharps disposal container, you may use a household container that is:
  - made of a heavy-duty plastic
  - can be closed with a tight-fitting, puncture-resistant lid, without sharps being able to come out
  - upright and stable during use
  - leak-resistant
  - properly labeled to warn of hazardous waste inside the container
- When your sharps disposal container is almost full, you will need to follow your community guidelines for the right way to dispose of your sharps disposal container. There may be state or local laws about how you should throw away used needles and syringes. Do not reuse or share your needles or syringes with other people. For more information about the safe sharps disposal, and for specific information about sharps disposal in the state that you live in, go to the FDA's website at: http://www.fda.gov/safesharpsdisposal.
- Do not dispose of your used sharps disposal container in your household trash unless your community guidelines permit this. Do not recycle your used sharps disposal container.

How should I store CAVERJECT IMPULSE?

1. Store unmixed CAVERJECT IMPULSE at room temperature between 68°F to 77°F (20°C to 25°C).
2. Store mixed CAVERJECT IMPULSE between 36°F to 77°F (2°C to 25°C). Do not freeze.
3. CAVERJECT IMPULSE should be used within 24 hours after it is mixed.

Keep CAVERJECT IMPULSE and all medicines out of the reach of children.

This Patient Information and Instructions for Use has been approved by the U.S Food and Drug Administration.

LAB-1504-2.0

Revised January 2023

PRINCIPAL DISPLAY PANEL - 10 microgram Syringe Label

NDC 63539-121-10

Caverject Impulse®
Dual Chamber System
alprostadil for injection

10 micrograms

KEEP OUT OF REACH OF CHILDREN
PROFESSIONAL SAMPLE - NOT FOR SALE

U.S. Pharmaceuticals
Pfizer Inc, NY, NY 10017 - MADE IN BELGIUM

8Q4727

LOT/EXP

PRINCIPAL DISPLAY PANEL - 10 microgram Syringe Carton

Pfizer

Caverject Impulse®

alprostadil for injection

10 micrograms

NDC 63539-121-11
Contains 2 of NDC 63539-121-10

For intracavernosal use only
Dual Chamber System

Contains 2 single dose injection systems
Diluent Contains Benzyl Alcohol

PROFESSIONAL SAMPLE - NOT FOR SALE

Rx only

PRINCIPAL DISPLAY PANEL - 20 microgram Syringe Label

NDC 63539-221-20

Caverject Impulse®
Dual Chamber System
alprostadil for injection

20 micrograms

KEEP OUT OF REACH OF CHILDREN
PROFESSIONAL SAMPLE - NOT FOR SALE

U.S. Pharmaceuticals
Pfizer Inc, NY, NY 10017 - MADE IN BELGIUM

8Q4728

LOT/EXP

PRINCIPAL DISPLAY PANEL - 20 microgram Syringe Carton

Pfizer

Caverject Impulse®

alprostadil for injection

20 micrograms

NDC 63539-221-21
Contains 2 of NDC 63539-221-20

For intracavernosal use only
Dual Chamber System

Contains 2 single dose injection systems
Diluent Contains Benzyl Alcohol

PROFESSIONAL SAMPLE - NOT FOR SALE

Rx only